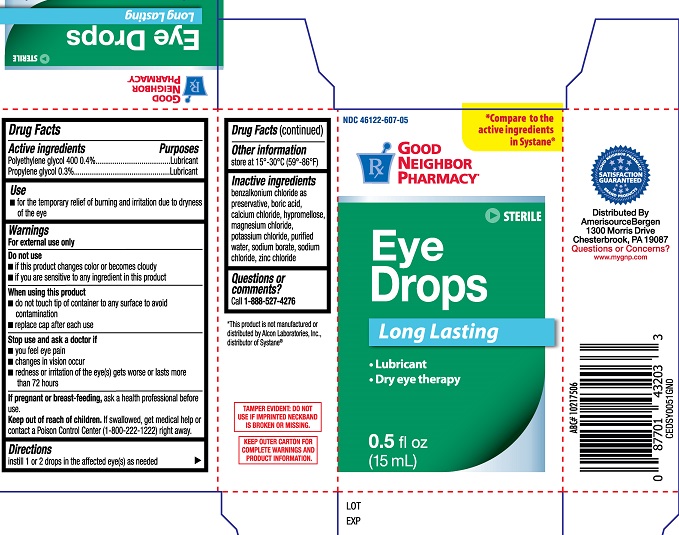 DRUG LABEL: GNP Eye Drops Long Lasting
NDC: 46122-607 | Form: SOLUTION
Manufacturer: AmerisourceBergen
Category: otc | Type: HUMAN OTC DRUG LABEL
Date: 20231223

ACTIVE INGREDIENTS: POLYETHYLENE GLYCOL 400 0.4 g/100 mL; PROPYLENE GLYCOL 0.3 g/100 mL
INACTIVE INGREDIENTS: BENZALKONIUM CHLORIDE; BORIC ACID; CALCIUM CHLORIDE; MAGNESIUM CHLORIDE; POTASSIUM CHLORIDE; SODIUM BORATE; SODIUM CHLORIDE; ZINC CHLORIDE; WATER; HYPROMELLOSES

GNP Eye Drops Long Lasting (PLD)

Active ingredients

polyethylene glycol 400.....0.4%

propylene glycol.....0.3%

Purposes

Polyethylene glycol 400.....Lubricant

Propylene glycol.....Lubricant

Use

for the temporary relief of burning and irritation due to dryness of the eye

Warnings

for external use only

Do not use

- if this product changes color or becomes cloudy
- if you are sensitive to any ingredient in this product

When using this product

- do not touch tip of container to any surface to avoid contamination
- replace cap after each use

Stop use and ask a doctor if

- you feel eye pain
- changes in vision occur
- redness or irritation of the eye, gets worse or lasts more than 72 hours

PREGNANCY OR BREAST FEEDING

If pregnant or breast-feeding, ask a health professional before use.

Keep out of reach of children. If swallowed, get medical help or contact a Poison Control Center (1-800-222-1222) right away.

Directions

Instill 1 or 2 drops in the affected eye(s) as needed.

Other information

store at 15º-30ºC (59º-86ºF)

Inactive ingredients

benzalkonium chloride as preservative, boric acid, calcium chloride, hypromellose, magnesium chloride, potassium chloride, purified water, sodium borate, sodium chloride, zinc chloride

Questions or comments?

Call 1-800-527-4276